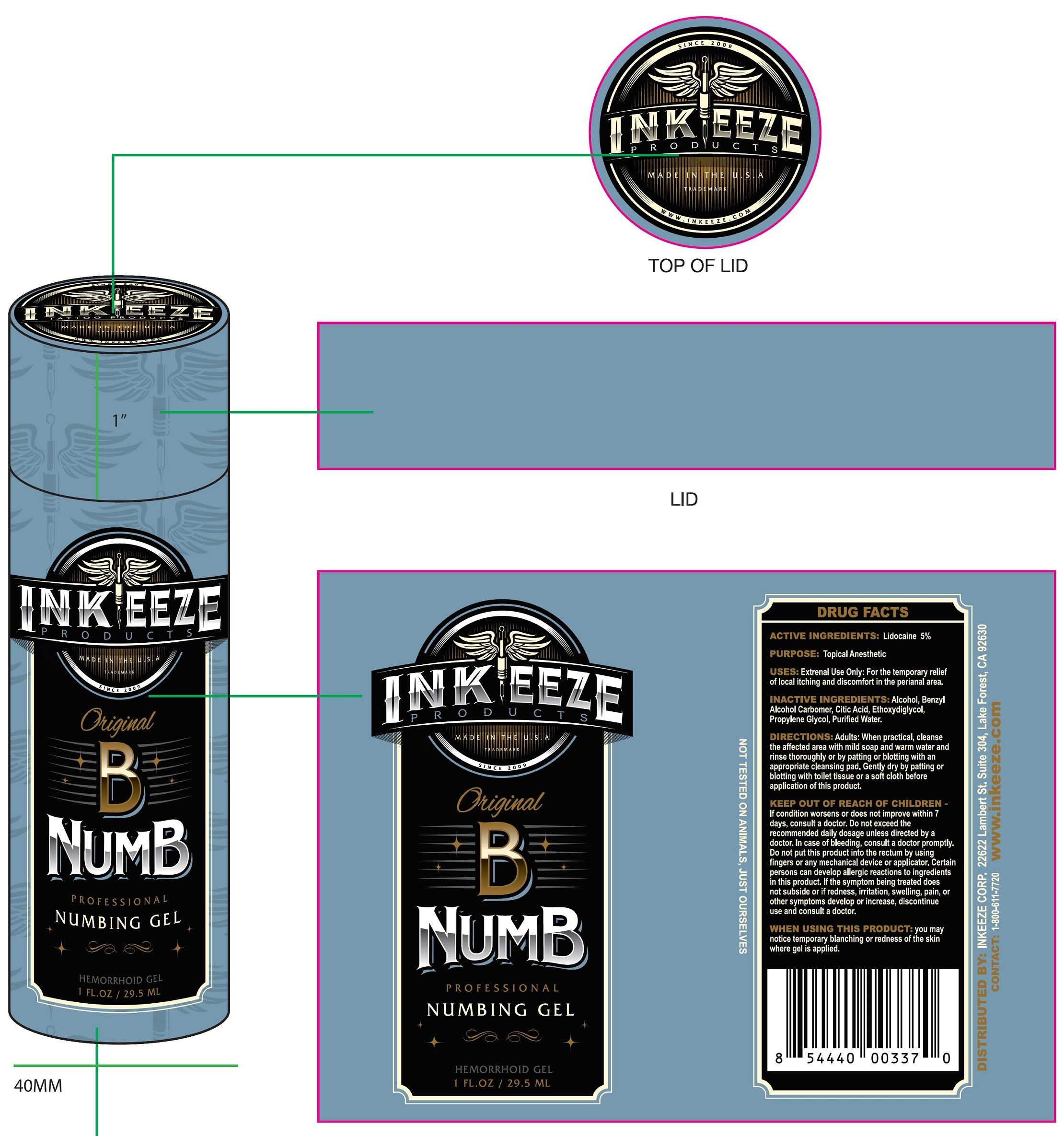 DRUG LABEL: Inkeeze Original B Numb Cylinder
NDC: 82022-001 | Form: GEL
Manufacturer: Indelicare, LLC
Category: otc | Type: HUMAN OTC DRUG LABEL
Date: 20210812

ACTIVE INGREDIENTS: LIDOCAINE 50 mg/1 mL
INACTIVE INGREDIENTS: ALCOHOL; BENZYL ALCOHOL; CARBOMER HOMOPOLYMER, UNSPECIFIED TYPE; CITRIC ACID MONOHYDRATE; DIETHYLENE GLYCOL MONOETHYL ETHER; PROPYLENE GLYCOL; WATER

Inkeeze Original Numb Professional Numbing Gel Cylinder

ACTIVE INGREDIENTS:

Lidocaine 5%

PURPOSE:

Topical Anesthetic

USES:

External Use Only: For the temporary relief of local itching and discomfort in the perianal area.

INACTIVE INGREDIENTS:

Alcohol, Benzyl Alcohol Carbomer, Citric Acid, Ethoxydiglycol, Propylene Glycol, Purified Water.

DIRECTIONS:

Adults: When practical, cleanse the affected area with mild soap and warm water and rinse thoroughly or by patting with an appropriate cleansing pad. Gently dry by patting or blotting with toilet tissue or a soft cloth before application of this product.

WARNINGS

KEEP OUT OF REACH OF CHILDREN

If condition worsens or does not improve within 7 days, consult a doctor. Do not exceed the recommended daily dosage unless directed by a doctor. In case of bleeding, consult a doctor promptly. Do not put this product into the rectum by using fingers or any mechanical device or applicator. Certain persons can develop allergic reactions to ingredients in this product. If the symptoms being treated does not subside or if redness, irritation, swelling, pain, or other symptoms develop or increase, discontinue use and consult a doctor.

WHEN USING THIS PRODUCT:

you may notice temporary blanching or redness of the skin where gel is applied.

CONTACT:

1-800-611-7720 www.inkeeze.com